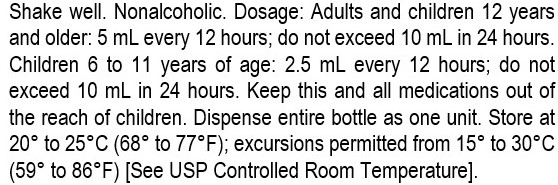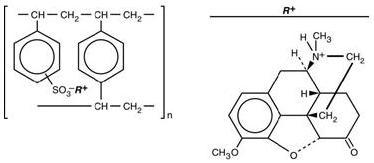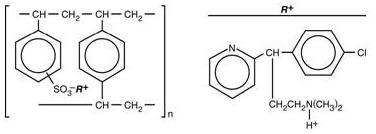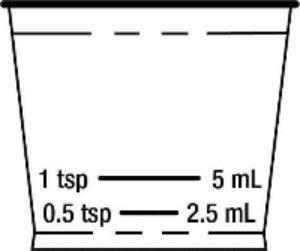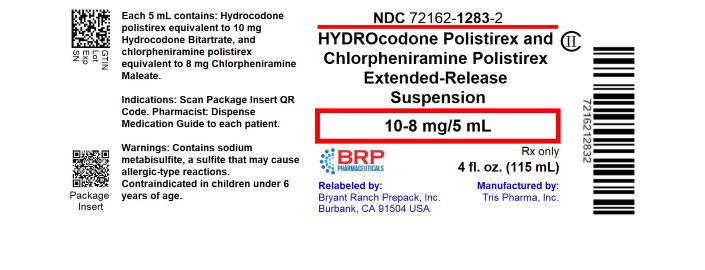 DRUG LABEL: Hydrocodone Polistirex and Chlorpheniramine Polistirex
NDC: 72162-1283 | Form: SUSPENSION, EXTENDED RELEASE
Manufacturer: Bryant Ranch Prepack
Category: prescription | Type: HUMAN PRESCRIPTION DRUG LABEL
Date: 20260122
DEA Schedule: CII

ACTIVE INGREDIENTS: HYDROCODONE BITARTRATE 10 mg/5 mL; CHLORPHENIRAMINE MALEATE 8 mg/5 mL
INACTIVE INGREDIENTS: ASCORBIC ACID; D&C YELLOW NO. 10; HIGH FRUCTOSE CORN SYRUP; METHYLPARABEN; POLYSORBATE 80; POLYVINYL ACETATE; PROPYLENE GLYCOL; PROPYLPARABEN; WATER; SODIUM ASCORBATE; SODIUM METABISULFITE; SODIUM POLYSTYRENE SULFONATE; SUCROSE; TRIACETIN; XANTHAN GUM; STARCH, CORN

HIGHLIGHTS OF PRESCRIBING INFORMATION

These highlights do not include all the information needed to use Hydrocodone Polistirex and Chlorpheniramine Polistirex Extended-Release Oral Suspension safely and effectively. See full prescribing information for Hydrocodone Polistirex and Chlorpheniramine Polistirex Extended-Release Oral Suspension.
Hydrocodone Polistirex and Chlorpheniramine Polistirex Extended-Release Suspension, for oral administration, CII
Initial U.S. Approval: 1987

WARNING: ADDICTION, ABUSE, AND MISUSE; LIFE-THREATENING RESPIRATORY DEPRESSION; ACCIDENTAL INGESTION; MEDICATION ERRORS; CYTOCHROME P450 3A4 INTERACTION; CONCOMITANT USE WITH BENZODIAZEPINES OR OTHER CNS DEPRESSANTS; INTERACTION WITH ALCOHOL; NEONATAL OPIOID WITHDRAWAL SYNDROME

See full prescribing information for complete boxed warning.

- Hydrocodone Polistirex and Chlorpheniramine Polistirex exposes users to risks of addiction, abuse, and misuse, which can lead to overdose and death. Assess patient’s risk before prescribing and monitor closely for these behaviors and conditions. (5.1)
- Serious, life-threatening, or fatal respiratory depression may occur. Monitor closely, especially upon initiation or when used in patients at higher risk. (5.2)
- Accidental ingestion of Hydrocodone Polistirex and Chlorpheniramine Polistirex, especially by children, can result in a fatal overdose of hydrocodone. (5.2)
- Ensure accuracy when prescribing, dispensing, and administering Hydrocodone Polistirex and Chlorpheniramine Polistirex. Dosing errors can result in accidental overdose and death. (2.1, 5.5)
- Concomitant use with CYP3A4 inhibitors (or discontinuation of CYP3A4 inducers) can result in a fatal overdose of hydrocodone. Avoid the use of Hydrocodone Polistirex and Chlorpheniramine Polistirex in patients taking CYP3A4 inhibitors or inducers. (5.7, 7.2, 7.3)
- Concomitant use of opioids with benzodiazepines or other central nervous system (CNS) depressants, including alcohol, may result in profound sedation, respiratory depression, coma, and death. Avoid the use of Hydrocodone Polistirex and Chlorpheniramine Polistirex in patients taking benzodiazepines, other CNS depressants, or alcohol. (5.8, 7.5)
- Instruct patients not to consume alcohol or any products containing alcohol while taking Hydrocodone Polistirex and Chlorpheniramine Polistirex because co-ingestion can result in fatal plasma hydrocodone levels. (5.8, 7.1)

Hydrocodone Polistirex and Chlorpheniramine Polistirex is not recommended for use in pregnant women. Prolonged use of Hydrocodone Polistirex and Chlorpheniramine Polistirex during pregnancy can result in neonatal opioid withdrawal syndrome, which may be life-threatening if not recognized and treated. If Hydrocodone Polistirex and Chlorpheniramine Polistirex is used for a prolonged period in a pregnant woman, advise the patient of the risk of neonatal opioid withdrawal syndrome and ensure that appropriate treatment will be available. (5.13, 8.1)

1 INDICATIONS AND USAGE

Hydrocodone Polistirex and Chlorpheniramine Polistirex is a combination of hydrocodone, an opioid agonist; and chlorpheniramine, a histamine-1 (H1) receptor antagonist, indicated for the temporary relief of cough and upper respiratory symptoms associated with allergy or the common cold in patients 18 years of age and older. (1)

Important Limitations of Use (1)

- Not indicated for pediatric patients under 18 years of age.
- Because of the risks of addiction, abuse, and misuse with opioids, even at recommended doses, reserve Hydrocodone Polistirex and Chlorpheniramine Polistirex for use in adult patients for whom the benefits of cough suppression are expected to outweigh the risks, and in whom an adequate assessment of the etiology of the cough has been made.

2 DOSAGE AND ADMINISTRATION

- Adults 18 years of age and older: 5 mL every 12 hours as needed, not to exceed 2 doses (10 mL) in 24 hours. (2.2)
- Measure Hydrocodone Polistirex and Chlorpheniramine Polistirex with an accurate milliliter measuring device. (2.1, 5.5)
- Do not increase the dose or dosing frequency. (2.1)
- Prescribe for the shortest duration consistent with treatment goals. (2.3)
- Reevaluate patients with unresponsive cough in 5 days or sooner for possible underlying pathology. (2.3)
- Reevaluate patient prior to refilling. (2.3)

3 DOSAGE FORMS AND STRENGTHS

Extended-release suspension: Each 5 mL contains hydrocodone polistirex equivalent to 10 mg of hydrocodone bitartrate; and chlorpheniramine polistirex equivalent to 8 mg of chlorpheniramine maleate. (3)

4 CONTRAINDICATIONS

- Children younger than 6 years of age. (4)
- Significant respiratory depression. (4)
- Acute or severe bronchial asthma in an unmonitored setting or in absence of resuscitative equipment. (4)
- Known or suspected gastrointestinal obstruction, including paralytic ileus.(4)
- Hypersensitivity to hydrocodone, chlorpheniramine, or any of the inactive ingredients in Hydrocodone Polistirex and Chlorpheniramine Polistirex. (4)

5 WARNINGS AND PRECAUTIONS

See Boxed WARNINGS

- Life-threatening respiratory depression in patients with chronic pulmonary disease or in elderly, cachectic, or debilitated patients: Monitor closely, particularly during initiation of therapy. (5.4)
- Activities requiring mental alertness: Avoid engaging in hazardous tasks requiring mental alertness such as driving or operating machinery. (5.6)
- Risks of use in patients with head injury, impaired consciousness, increased intracranial pressure, or brain tumors: Avoid use. May increase intracranial pressure and obscure the clinical course of head injuries. (5.10)
- Seizures in patients with seizure disorders: Monitor during therapy. (5.11)
- Severe hypotension: Monitor during initiation of therapy. Avoid use in patients with circulatory shock. (5.12)
- Adrenal insufficiency: If diagnosed, treat with physiologic replacement of corticosteroids, and wean patient off of the opioid. (5.14)

6 ADVERSE REACTIONS

Common adverse reactions include: Sedation (somnolence, mental clouding, lethargy), impaired mental and physical performance, lightheadedness, dizziness, headache, dry mouth, nausea, vomiting, and constipation (6)

To report SUSPECTED ADVERSE REACTIONS, contact Tris Pharma, Inc. at 1-732-940-0358 or FDA at 1-800-FDA-1088 or www.fda.gov/medwatch.

7 DRUG INTERACTIONS

- Phenytoin: Avoid concomitant use; may increase phenytoin levels. (7.4)
  Serotonergic drugs: Concomitant use may result in serotonin syndrome.

- Discontinue if serotonin syndrome is suspected. (7.6)
- Monoamine Oxidase Inhibitors (MAOIs): Can potentiate the effects of hydrocodone. Avoid concomitant use in patients receiving MAOIs or within 14 days of stopping an MAOI. (7.7)
- Muscle relaxants: Avoid concomitant use. (7.8)
- Diuretics: Hydrocodone may reduce the efficacy of diuretics. Monitor for reduced effect. (7.9)
- Anticholinergic drugs: Concomitant use may cause paralytic ileus. (5.9, 7.10)

8 USE IN SPECIFIC POPULATIONS

- Pregnancy: Avoid use in pregnant women. May cause fetal harm. (8.1)
- Lactation: Breastfeeding not recommended. (8.2)
- Renal Impairment: Use with caution in patients with severe renal impairment. (8.6)

- Hepatic Impairment: Use with caution in patients with severe hepatic impairment. (8.7)

FULL PRESCRIBING INFORMATION

WARNING: ADDICTION, ABUSE, AND MISUSE; LIFE-THREATENING RESPIRATORY DEPRESSION; ACCIDENTAL INGESTION; MEDICATION ERRORS; CYTOCHROME P450 3A4 INTERACTION; CONCOMITANT USE WITH BENZODIAZEPINES OR OTHER CNS DEPRESSANTS; INTERACTION WITH ALCOHOL; NEONATAL OPIOID WITHDRAWAL SYNDROME

Addiction, Abuse, and Misuse

Hydrocodone Polistirex and Chlorpheniramine Polistirex exposes patients and other users to the risks of opioid addiction, abuse, and misuse, which can lead to overdose and death. Reserve Hydrocodone Polistirex and Chlorpheniramine Polistirex for use in adult patients for whom the benefits of cough suppression are expected to outweigh the risks, and in whom an adequate assessment of the etiology of the cough has been made. Assess each patient’s risk prior to prescribing Hydrocodone Polistirex and Chlorpheniramine Polistirex, prescribe Hydrocodone Polistirex and Chlorpheniramine Polistirex for the shortest duration that is consistent with individual patient treatment goals, monitor all patients regularly for the development of addition or abuse, and refill only after reevaluation of the need for continued treatment. [see Warnings and Precautions (5.1)]

Life-Threatening Respiratory Depression

Serious, life-threatening, or fatal respiratory depression may occur with use of Hydrocodone Polistirex and Chlorpheniramine Polistirex. Monitor for respiratory depression, especially during initiation of Hydrocodone Polistirex and Chlorpheniramine Polistirex therapy or when used in patients at higher risk [see Warnings and Precautions (5.2)].

Accidental Ingestion

Accidental ingestion of even one dose of Hydrocodone Polistirex and Chlorpheniramine Polistirex, especially by children, can result in a fatal overdose of hydrocodone [see Warnings and Precautions (5.2)].

Risk of Medication Errors

Ensure accuracy when prescribing, dispensing, and administering Hydrocodone Polistirex and Chlorpheniramine Polistirex. Dosing errors can result in accidental overdose and death. Always use an accurate milliliter measuring device when measuring and administering Hydrocodone Polistirex and Chlorpheniramine Polistirex [see Dosage and Administration (2.1), Warnings and Precautions (5.5)].

Cytochrome P450 3A4 Interaction

The concomitant use of Hydrocodone Polistirex and Chlorpheniramine Polistirex with all cytochrome P450 3A4 inhibitors may result in an increase in hydrocodone plasma concentrations, which could increase or prolong adverse drug effects and may cause potentially fatal respiratory depression. In addition, discontinuation of a concomitantly used cytochrome P450 3A4 inducer may result in an increase in hydrocodone plasma concentration. Avoid the use of Hydrocodone Polistirex and Chlorpheniramine Polistirex in patients taking a CYP3A4 inhibitor or inducer [see Warnings and Precautions (5.7), Drug Interactions (7.2, 7.3)].

Risks from Concomitant Use with Benzodiazepines or Other CNS Depressants

Concomitant use of opioids with benzodiazepines or other central nervous system (CNS) depressants, including alcohol, may result in profound sedation, respiratory depression, coma, and death. Avoid the use of Hydrocodone Polistirex and Chlorpheniramine Polistirex in patients taking benzodiazepines, other CNS depressants, or alcohol [see Warning and Precautions (5.8), Drug Interactions (7.5)].

Interaction with Alcohol

Instruct patients not to consume alcoholic beverages or use prescription or non-prescription products that contain alcohol while taking Hydrocodone Polistirex and Chlorpheniramine Polistirex. The co-ingestion of alcohol with Hydrocodone Polistirex and Chlorpheniramine Polistirex may result in increased plasma levels and a potentially fatal overdose of hydrocodone [see Warnings and Precautions (5.8) and Drug Interactions (7.1)].

Neonatal Opioid Withdrawal Syndrome

Hydrocodone Polistirex and Chlorpheniramine Polistirex is not recommended for use in pregnant women [see Use in Specific Populations (8.1)]. Prolonged use of Hydrocodone Polistirex and Chlorpheniramine Polistirex during pregnancy can result in neonatal opioid withdrawal syndrome, which may be life-threatening if not recognized and treated, and requires management according to protocols developed by neonatology experts. If Hydrocodone Polistirex and Chlorpheniramine Polistirex is used for a prolonged period in a pregnant woman, advise the patient of the risk of neonatal opioid withdrawal syndrome and ensure that appropriate treatment will be available [see Warnings and Precautions (5.13)].

1 INDICATIONS AND USAGE

Hydrocodone Polistirex and Chlorpheniramine Polistirex Extended-Release Suspension is indicated for the temporary relief of cough and upper respiratory symptoms associated with allergy or the common cold in patients 18 years of age and older.

Important Limitations of Use:

• Not indicated for pediatric patients under 18 years of age [see Use in Specific Populations (8.4)].

• Contraindicated in pediatric patients less than 6 years of age [see Contraindications (4)].

• Because of the risks of addiction, abuse, and misuse with opioids, even at recommended doses [see Warnings and Precautions (5.1)], reserve Hydrocodone Polistirex and Chlorpheniramine Polistirex for use in adult patients for whomthe benefits of cough suppression are expected to outweigh the risks, and in whom an adequateassessment of the etiology of the cough has been made.

2 DOSAGE AND ADMINISTRATION

2.1 Important Dosage and Administration Instructions

Administer Hydrocodone Polistirex and Chlorpheniramine Polistirex Extended-Release Suspension by the oral route only. Hydrocodone Polistirex and Chlorpheniramine Polistirex Extended-Release Suspension can be taken with or without food. Shake well before using. Do not mix Hydrocodone Polistirex and Chlorpheniramine Polistirex Extended-Release Suspension with other liquids or medicines. Mixing may change how Hydrocodone Polistirex and Chlorpheniramine Polistirex Extended-Release Suspension works.

Always use an accurate milliliter measuring device when administering Hydrocodone Polistirex and Chlorpheniramine Polistirex Extended-Release Suspension to ensure that the dose is measured and administered accurately. A household teaspoon is not an accurate measuring device and could lead to overdosage [see Warnings and Precautions (5.5)]. The dosing cup is provided with the 3 oz (70 mL) and 4 oz (115 mL) packaged product. The dosing cup fills for 2.5 mL dose and for 5 mL dose. Instruct the patient to fill to the line that the dose has been prescribed. Do not fill over the dose prescribed. Rinse the measuring cup with water after each use. For prescriptions where a measuring device is not provided, a pharmacist can provide an appropriate measuring device and can provide instructions for measuring the correct dose. Do not overfill. Rinse the measuring device with water after each use.

Advise patients not to increase the dose or dosing frequency of Hydrocodone Polistirex and Chlorpheniramine Polistirex Extended-Release Suspension because serious adverse events such as respiratory depression may occur with overdosage [see Warnings and Precautions (5.2) and Overdosage (10)]. The dosage of Hydrocodone Polistirex and Chlorpheniramine Polistirex Extended-Release Suspension should not be increased if cough fails to respond; an unresponsive cough should be reevaluated for possible underlying pathology [see Dosage and Administration (2.3) and Warnings and Precautions (5.4)].

2.2 Recommended Dosage

Adults 18 years of age and older: 5 mL every 12 hours as needed, not to exceed 2 doses (10 mL) in 24 hours

2.3 Monitoring, Maintenance, and Discontinuation of Therapy

Prescribe Hydrocodone Polistirex and Chlorpheniramine Polistirex Extended-Release Suspension for the shortest duration that is consistent with individual patient treatment goals [see Warnings and Precautions (5.1)].

Monitor patients closely for respiratory depression, especially within the first 24 to 72 hours of initiating therapy [see Warnings and Precautions (5.2)].

Reevaluate patients with unresponsive cough in 5 days or sooner for possible underlying pathology, such as foreign body or lower respiratory tract disease [see Warnings and Precautions (5.4)]. If a patient requires a refill, reevaluate the cause of the cough and assess the need for continued treatment with Hydrocodone Polistirex and Chlorpheniramine Polistirex Extended-Release Suspension, the relative incidence of adverse reactions, and the development of addiction, abuse, or misuse [see Warnings and Precautions (5.1)].

Do not abruptly discontinue Hydrocodone Polistirex and Chlorpheniramine Polistirex Extended-Release Suspension in a physically-dependent patient [see Drug Abuse and Dependence (9.3)]. When a patient who has been taking Hydrocodone Polistirex and Chlorpheniramine Polistirex Extended-Release Suspension regularly and may bephysically dependent no longer requires therapy with Hydrocodone Polistirex and Chlorpheniramine Polistirex Extended-Release Suspension, taper the dose gradually, by25% to 50% every 2 to 4 days, while monitoring carefully for signs and symptoms of withdrawal. If the patientdevelops these signs or symptoms, raise the dose to the previous level and taper more slowly, either byincreasing the interval between decreases, decreasing the amount of change in dose, or both.

3 DOSAGE FORMS AND STRENGTHS

Extended-release suspension: Each 5 mL contains hydrocodone polistirex, which contains 6.66 mg of hydrocodone (equivalent to 10 mg of hydrocodone bitartrate); and chlorpheniramine polistirex, which contains 5.62 mg of chlorpheniramine (equivalent to 8 mg of chlorpheniramine maleate). Hydrocodone Polistirex and Chlorpheniramine Polistirex Extended-Release Suspension is a yellow-colored suspension [see Description (11)].

4 CONTRAINDICATIONS

Hydrocodone Polistirex and Chlorpheniramine Polistirex is contraindicated for:

- All children younger than 6 years of age [see Warnings and Precautions (5.2, 5.3), Use in Specific Populations (8.4)].

Hydrocodone Polistirex and Chlorpheniramine Polistirex is also contraindicated in patients with:

- Significant respiratory depression [see Warnings and Precautions (5.2)].
- Acute or severe bronchial asthma in an unmonitored setting or in the absence of resuscitative equipment[see Warnings and Precautions (5.4)].
- Known or suspected gastrointestinal obstruction, including paralytic ileus [see Warnings and Precautions (5.9)].
- Hypersensitivity to hydrocodone, chlorpheniramine, or any of the inactive ingredients in Hydrocodone Polistirex and Chlorpheniramine Polistirex [see Adverse Reactions (6)].

5 WARNINGS AND PRECAUTIONS

5.1 Addiction, Abuse, and Misuse

Hydrocodone Polistirex and Chlorpheniramine Polistirex contains hydrocodone, a Schedule II controlled substance. As an opioid, Hydrocodone Polistirex and Chlorpheniramine Polistirex exposes users to the risks of addiction, abuse, and misuse [see Drug Abuse and Dependence (9)], which can lead to overdose and death [see Overdosage (10)]. Reserve Hydrocodone Polistirex and Chlorpheniramine Polistirex Extended-Release Suspension for use in adult patients for whom the benefits of cough suppression are expected to outweigh the risks, and in whom an adequate assessment of the etiology of the cough has been made. Assess each patient’s risk prior to prescribing Hydrocodone Polistirex and Chlorpheniramine Polistirex Extended-Release Suspension, prescribe Hydrocodone Polistirex and Chlorpheniramine Polistirex Extended-Release Suspension for the shortest duration that is consistent with individual patient treatment goals, monitor all patients regularly for the development of addiction or abuse, and refill only after reevaluation of the need for continued treatment.

Although the risk of addiction in any individual is unknown, it can occur in patients appropriately prescribed Hydrocodone Polistirex and Chlorpheniramine Polistirex. Addiction can occur at recommended dosages and if the drug is misused or abused. Risks are increased in patients with a personal or family history of substance abuse (including drug or alcohol abuse or addiction) or mental illness (e.g., major depression).

Opioids are sought by drug abusers and people with addiction disorders and are subject to criminal diversion. Consider these risks when prescribing or dispensing Hydrocodone Polistirex and Chlorpheniramine Polistirex. Strategies to reduce these risks include prescribing the drug in the smallest appropriate quantity and advising the patient on the proper disposal of unused drug [see Patient Counseling Information (17)]. Contact local state professional licensing board or state controlled substances authority for information on how to prevent and detect abuse or diversion of this product.

5.2 Life-Threatening Respiratory Depression

Serious, life-threatening, or fatal respiratory depression has been reported with the use of opioids, including hydrocodone, one of the active ingredients in Hydrocodone Polistirex and Chlorpheniramine Polistirex. Hydrocodone produces dose-related respiratory depression by directly acting on the brain stem respiratory center that controls respiratory rhythm and may produce irregular and periodic breathing. Respiratory depression, if not immediately recognized and treated, may lead to respiratory arrest and death. Management of respiratory depression includes discontinuation of Hydrocodone Polistirex and Chlorpheniramine Polistirex, close observation, supportive measures, and use of opioid antagonists (e.g. naloxone), depending on the patient’s clinical status [see Overdosage (10)]. Carbon dioxide (CO2) retention from opioid-induced respiratory depression can exacerbate the sedating effects of opioids.

While serious, life-threatening, or fatal respiratory depression can occur at any time during the use of Hydrocodone Polistirex and Chlorpheniramine Polistirex, the risk is greatest during the initiation of therapy, when Hydrocodone Polistirex and Chlorpheniramine Polistirex is used concomitantly with other drugs that may cause respiratory depression [see Warnings and Precautions (5.8)], in patients with chronic pulmonary disease or decreased respiratory reserve, and in patients with altered pharmacokinetics or altered clearance (e.g. elderly, cachectic, or debilitated patients) [see Warnings and Precautions (5.4)].

To reduce the risk of respiratory depression, proper dosing of Hydrocodone Polistirex and Chlorpheniramine Polistirex is essential [see Dosage and Administration (2.1), Warnings and Precautions (5.5)]. Monitor patients closely, especially within the first 24 to 72 hours of initiating therapy or when used in patients at higher risk.

Overdose of hydrocodone in adults has been associated with fatal respiratory depression, and the use of hydrocodone in children younger than 6 years of age has been associated with fatal respiratory depression when used as recommended. Accidental ingestion of even one dose of Hydrocodone Polistirex and Chlorpheniramine Polistirex, especially by children, can result in respiratory depression and death.

5.3 Risks of Use in Pediatric Populations

Children are particularly sensitive to the respiratory depressant effects of hydrocodone [see Warnings and Precautions (5.2)]. Because of the risk of life-threatening respiratory depression and death, Hydrocodone Polistirex and Chlorpheniramine Polistirex is contraindicated in children less than 6 years of age [see Contraindications (4)].

Use of Hydrocodone Polistirex and Chlorpheniramine Polistirex in children also exposes them to the risks of addiction, abuse, and misuse [see Drug Abuse and Dependence (9)], which can lead to overdose and death [see Warnings and Precautions (5.1), Overdosage (10)]. Because the benefits of symptomatic treatment of cough associated with allergies or thecommon cold do not outweigh the risks of use of hydrocodone in pediatric patients, Hydrocodone Polistirex and Chlorpheniramine Polistirexis not indicated for use in patients younger than 18 years of age [see Indications (1), Use in Specific Populations (8.4)].

5.4 Risks of Use in Other At-Risk Populations

Unresponsive Cough

The dosage of Hydrocodone Polistirex and Chlorpheniramine Polistirex should not be increased if cough fails to respond; an unresponsive cough should be reevaluated in 5 days or sooner for possible underlying pathology, such as foreign body or lower respiratory tract disease [see Dosage and Administration (2.3)].

Asthma and Other Pulmonary Disease

The use of Hydrocodone Polistirex and Chlorpheniramine Polistirex in patients with acute or severe bronchial asthma in an unmonitored setting or in the absence of resuscitative equipment is contraindicated [see Contraindications (4)].

Opioid analgesics and antitussives, including hydrocodone, one of the active ingredients in Hydrocodone Polistirex and Chlorpheniramine Polistirex, should not be used in patients with acute febrile illness associated with productive cough or in patients with chronic respiratory disease where interference with ability to clear the tracheobronchial tree of secretions would have a deleterious effect on the patient’s respiratory function.

Hydrocodone Polistirex and Chlorpheniramine Polistirex-treated patients with significant chronic obstructive pulmonary disease or corpulmonale, and those with a substantially decreased respiratory reserve, hypoxia, hypercapnia, or pre-existing respiratory depression are at increased risk of decreased respiratory drive including apnea, even at recommended dosages of Hydrocodone Polistirex and Chlorpheniramine Polistirex [see Warnings and Precautions (5.2)].

Elderly, Cachectic, or Debilitated Patients: Life-threatening respiratory depression is more likely to occur in elderly, cachectic, or debilitated patients because they may have altered pharmacokinetics or altered clearance compared to younger, healthier patients [see Warnings and Precautions (5.2)].

Because of the risk of respiratory depression, avoid the use of opioid antitussives, including Hydrocodone Polistirex and Chlorpheniramine Polistirex in patients with compromised respiratory function, patients at risk of respiratory failure, and in elderly, cachectic, or debilitated patients. If Hydrocodone Polistirex and Chlorpheniramine Polistirex is prescribed, monitor such patients closely, particularly when initiating Hydrocodone Polistirex and Chlorpheniramine Polistirex and when Hydrocodone Polistirex and Chlorpheniramine Polistirex is given concomitantly with other drugs that depress respiration [see Warnings and Precautions (5.8)].

5.5 Risk of Accidental Overdose and Death due to Medication Errors

Dosing errors can result in accidental overdose and death. To reduce the risk of overdose and respiratory depression, ensure that the dose of Hydrocodone Polistirex and Chlorpheniramine Polistirex is communicated clearly and dispensed accurately [see Dosage and Administration (2.1)].

Advise patients to always use an accurate milliliter measuring device when measuring and administering Hydrocodone Polistirex and Chlorpheniramine Polistirex. Inform patients that household teaspoon is not an accurate measuring device and such use could lead to overdosage and serious adverse reactions [see Overdosage (10)]. For prescriptions where a measuring device is not provided, a pharmacist can provide an appropriate calibrated measuring device and can provide instructions for measuring the correct dose.

5.6 Activities Requiring Mental Alertness: Risks of Driving and Operating Machinery

Hydrocodone and chlorpheniramine, two of the active ingredients in Hydrocodone Polistirex and Chlorpheniramine Polistirex, may produce marked drowsiness and impair the mental and/or physical abilities required for the performance of potentially hazardous tasks such as driving a car or operating machinery. Advise patients to avoid engaging in hazardous tasks requiring mental alertness and motor coordination after ingestion of Hydrocodone Polistirex and Chlorpheniramine Polistirex. Avoid concurrent use of Hydrocodone Polistirex and Chlorpheniramine Polistirex with alcohol or other central nervous system depressants because additional impairment of central nervous system performance may occur [see Warnings and Precautions (5.8)].

5.7 Risks from Concomitant Use or Discontinuation of Cytochrome P450 3A4 Inhibitors and Inducers

Concomitant use of Hydrocodone Polistirex and Chlorpheniramine Polistirex with a CYP3A4 inhibitor, such as macrolide antibiotics (e.g., erythromycin), azole-antifungal agents (e.g., ketoconazole), and protease inhibitors (e.g., ritonavir), may increase plasma concentrations of hydrocodone and prolong opioid adverse reactions, which may cause potentially fatal respiratory depression [see Warnings and Precautions (5.2)], particularly when an inhibitor is added after a stable dose of Hydrocodone Polistirex and Chlorpheniramine Polistirex is achieved. Similarly, discontinuation of a CYP3A4 inducer, such as rifampin, carbamazepine, and phenytoin, in Hydrocodone Polistirex and Chlorpheniramine Polistirex-treated patients may increase hydrocodone plasma concentrations and prolong opioid adverse reactions.

Concomitant use of Hydrocodone Polistirex and Chlorpheniramine Polistirex with CYP3A4 inducers or discontinuation of an CYP3A4 inhibitor could decrease hydrocodone plasma concentrations, decrease opioid efficacy or, possibly, lead to a withdrawal syndrome in a patient who had developed physical dependence to hydrocodone.

Avoid the use of Hydrocodone Polistirex and Chlorpheniramine Polistirex in patients who are taking a CYP3A4 inhibitor or inducer. If concomitant use of Hydrocodone Polistirex and Chlorpheniramine Polistirex with a CYP3A4 inhibitor or inducer is necessary, monitor patients for signs and symptoms that may reflect opioid toxicity and opioid withdrawal [see Drug Interactions (7.2, 7.3)].

5.8 Risks from Concomitant Use with Benzodiazepines or other CNS Depressants

Concomitant use of opioids, including Hydrocodone Polistirex and Chlorpheniramine Polistirex, with benzodiazepines, or other CNS depressants, including alcohol, may result in profound sedation, respiratory depression, coma, and death. Because of these risks, avoid use of opioid cough medications in patients taking benzodiazepines, other CNS depressants, or alcohol [see Drug Interactions (7.1, 7.5)].

Observational studies have demonstrated that concomitant use of opioid analgesics and benzodiazepines increases the risk of drug-related mortality compared to use of opioids alone. Because of similar pharmacologic properties, it is reasonable to expect similar risk with concomitant use of opioid cough medications and benzodiazepines, other CNS depressants, or alcohol.

Advise both patients and caregivers about the risks of respiratory depression and sedation if Hydrocodone Polistirex and Chlorpheniramine Polistirex is used with benzodiazepines, alcohol, or other CNS depressants [see Patient Counseling Information (17)].

Patients must not consume alcoholic beverages, or prescription or non-prescription products containing alcohol, while on Hydrocodone Polistirex and Chlorpheniramine Polistirex therapy. The co-ingestion of alcohol with Hydrocodone Polistirex and Chlorpheniramine Polistirex may result in increased plasma levels and a potentially fatal overdose of hydrocodone [see Drug Interactions (7.1)].

5.9 Risks of Use in Patients with Gastrointestinal Conditions

Hydrocodone Polistirex and Chlorpheniramine Polistirex is contraindicated in patients with known or suspected gastrointestinal obstruction, including paralytic ileus [see Contraindications (4)]. The use of hydrocodone in Hydrocodone Polistirex and Chlorpheniramine Polistirex may obscure the diagnosis or clinical course of patients with acute abdominal conditions.

The concurrent use of anticholinergics with Hydrocodone Polistirex and Chlorpheniramine Polistirex may produce paralytic ileus [see Drug Interactions (7.10)].

The hydrocodone in Hydrocodone Polistirex and Chlorpheniramine Polistirex may result in constipation or obstructive bowel disease, especially in patients with underlying intestinal motility disorders. Use with caution in patients with underlying intestinal motility disorders.

The hydrocodone in Hydrocodone Polistirex and Chlorpheniramine Polistirex may cause spasm of the sphincter of Oddi, resulting in an increase in biliary tract pressure. Opioids may cause increases in serum amylase [see Warnings and Precautions (5.15)]. Monitor patients with biliary tract disease, including acute pancreatitis for worsening symptoms.

5.10 Risks of Use in Patients with Head Injury, Impaired Consciousness, Increased Intracranial Pressure, or Brain Tumors

Avoid the use of Hydrocodone Polistirex and Chlorpheniramine Polistirex in patients with head injury, intracranial lesions, or a pre-existing increase in intracranial pressure. In patients who may be susceptible to the intracranial effects of CO2 retention (e.g., those with evidence of increased intracranial pressure or brain tumors), Hydrocodone Polistirex and Chlorpheniramine Polistirex may reduce respiratory drive, and the resultant CO2 retention can further increase intracranial pressure. Furthermore, opioids produce adverse reactions that may obscure the clinical course of patients with head injuries.

5.11 Increased Risk of Seizures in Patients with Seizure Disorders

The hydrocodone and chlorpheniramine in Hydrocodone Polistirex and Chlorpheniramine Polistirex may increase the frequency of seizures in patients with seizure disorders, and may increase the risk of seizures occurring in other clinical settings associated with seizures. Monitor patients with a history of seizure disorders for worsened seizure control during Hydrocodone Polistirex and Chlorpheniramine Polistirex therapy.

5.12 Severe Hypotension

Hydrocodone Polistirex and Chlorpheniramine Polistirex may cause severe hypotension including orthostatic hypotension and syncope in ambulatory patients. There is increased risk in patients whose ability to maintain blood pressure has already been compromised by a reduced blood volume or concurrent administration of certain CNS depressant drugs (e.g., phenothiazines or general anesthetics) [see Drug Interactions (7.5)]. Monitor these patients for signs of hypotension after initiating Hydrocodone Polistirex and Chlorpheniramine Polistirex.

In patients with circulatory shock, Hydrocodone Polistirex and Chlorpheniramine Polistirex may cause vasodilation that can further reduce cardiac output and blood pressure. Avoid the use of Hydrocodone Polistirex and Chlorpheniramine Polistirex in patients with circulatory shock.

5.13 Neonatal Opioid Withdrawal Syndrome

Hydrocodone Polistirex and Chlorpheniramine Polistirex is not recommended for use in pregnant women. Prolonged use of Hydrocodone Polistirex and Chlorpheniramine Polistirex during pregnancy can result in withdrawal in the neonate. Neonatal opioid withdrawal syndrome, unlike opioid withdrawal syndrome in adults, may be life-threatening if not recognized and treated, and requires management according to protocols developed by neonatology experts. Observe newborns for signs of neonatal opioid withdrawal syndrome and manage accordingly. Advise pregnant women using opioids for a prolonged period of the risk of neonatal opioid withdrawal syndrome and ensure that appropriate treatment will be available [see Use in Specific Populations (8.1), Patient Counseling Information (17)].

5.14 Adrenal Insufficiency

Cases of adrenal insufficiency have been reported with opioid use, more often following greater than one month of use. Presentation of adrenal insufficiency may include non-specific symptoms and signs including nausea, vomiting, anorexia, fatigue, weakness, dizziness, and low blood pressure. If adrenal insufficiency is suspected, confirm the diagnosis with diagnostic testing as soon as possible. If adrenal insufficiency is diagnosed, treat with physiologic replacement doses of corticosteroids. Wean the patient off of the opioid to allow adrenal function to recover and continue corticosteroid treatment until adrenal function recovers. Other opioids may be tried as some cases reported use of a different opioid without recurrence of adrenal insufficiency. The information available does not identify any particular opioids as being more likely to be associated with adrenal insufficiency.

5.15 Drug/Laboratory Test Interactions

Because opioid agonists may increase biliary tract pressure, with resultant increase in plasma amylase or lipase levels, determination of these enzyme levels may be unreliable for 24 hours after administration of a dose of Hydrocodone Polistirex and Chlorpheniramine Polistirex.

6 ADVERSE REACTIONS

The following serious adverse reactions are described, or described in greater detail, in other sections:

• Addiction, abuse, and misuse [see Warnings and Precautions (5.1), Drug Abuse and Dependence (9.3)]

• Life-threatening respiratory depression [see Warnings and Precautions (5.2, 5.3,5.4, 5.8), Overdosage (10)]

• Accidental overdose and death due to medication errors [see Warnings and Precautions (5.5)]

• Decreased mental alertness with impaired mental and/or physical abilities [see Warnings and Precautions (5.6)]

• Interactions with benzodiazepines and other CNS depressants [see Warnings and Precautions (5.8), Drug Interactions (7.1, 7.5)]

• Paralytic ileus, gastrointestinal adverse reactions [see Warnings and Precautions (5.9)]

• Increased intracranial pressure [see Warnings and Precautions (5.10)]

• Obscured clinical course in patients with head injuries [see Warnings and Precautions (5.10)]

• Seizures [see Warnings and Precautions (5.11)]

• Severe hypotension [see Warnings and Precautions (5.12)]

• Neonatal Opioid Withdrawal Syndrome [see Warnings and Precautions (5.13)]

• Adrenal insufficiency [see Warnings and Precautions (5.14)]

The following adverse reactions have been identified during clinical studies, in the literature, or during post-approval use of hydrocodone and/or chlorpheniramine. Because these reactions may be reported voluntarily from a population of uncertain size, it is not always possible to reliably estimate their frequency or establish a causal relationship to drug exposure.

The most common adverse reactions to Hydrocodone Polistirex and Chlorpheniramine Polistirex include: Sedation (somnolence, mental clouding, lethargy), impaired mental and physical performance, lightheadedness, dizziness, headache, dry mouth, nausea, vomiting, and constipation.

Other reactions include:

Anaphylaxis: Anaphylaxis has been reported with hydrocodone, one of the ingredients in Hydrocodone Polistirex and Chlorpheniramine Polistirex.

Body as a whole: Coma, death, fatigue, falling injuries, lethargy.

Cardiovascular: Peripheral edema, increased blood pressure, decreased blood pressure, tachycardia, chest pain, palpitation, syncope, orthostatic hypotension, prolonged QT interval, hot flush.

Central Nervous System: Ataxia, facial dyskinesia, insomnia, migraine, increased intracranial pressure, seizure, tremor, tinnitus, vertigo.

Dermatologic: Flushing, hyperhidrosis, pruritus, rash.

Endocrine/Metabolic: Cases of serotonin syndrome, a potentially life-threatening condition, have been reported during concomitant use of opioids with serotonergic drugs. Cases of adrenal insufficiency have been reported with opioid use, more often following greater than one month of use. Cases of androgen deficiency have occurred with chronic use of opioids [see Clinical Pharmacology (12.2)].

Gastrointestinal: Abdominal pain, bowel obstruction, decreased appetite, diarrhea, difficulty swallowing, GERD, indigestion, pancreatitis, paralytic ileus, biliary tract spasm (spasm of the sphincter of Oddi).

Genitourinary: Urinary tract infection, ureteral spasm, spasm of vesicle sphincters, urinary retention.

Hematologic: Agranulocytosis, aplastic anemia, and thrombocytopenia have been reported.

Laboratory: Increases in serum amylase.

Musculoskeletal: Arthralgia, backache, muscle spasm.

Ophthalmic: Blurred vision, diplopia, miosis (constricted pupils), visual disturbances.

Psychiatric: Agitation, anxiety, confusion, fear, dysphoria, depression, hallucinations.

Reproductive: Hypogonadism, infertility.

Respiratory: Bronchitis, cough, dyspnea, nasal congestion, nasopharyngitis, respiratory depression, sinusitis, upper respiratory tract infection, thickening of bronchial secretions, tightness of chest and wheezing, dry nose, dry throat.

Other: Drug abuse, drug dependence, opioid withdrawal syndrome.

7 DRUG INTERACTIONS

No specific drug interaction studies have been conducted with Hydrocodone Polistirex and Chlorpheniramine Polistirex.

7.1 Alcohol

Concomitant use of alcohol with Hydrocodone Polistirex and Chlorpheniramine Polistirex can result in an increase of hydrocodone plasma levels and potentially fatal overdose of hydrocodone. Instruct patients not to consume alcoholic beverages or use prescription or nonprescription products containing alcohol while on Hydrocodone Polistirex and Chlorpheniramine Polistirex therapy [see Warnings and Precautions (5.8), Clinical Pharmacology (12.3)].

7.2 Inhibitors of CYP3A4 and CYP2D6

The concomitant use of Hydrocodone Polistirex and Chlorpheniramine Polistirex and CYP3A4 inhibitors, such as macrolide antibiotics (e.g., erythromycin), azole-antifungal agents (e.g. ketoconazole), or protease inhibitors (e.g., ritonavir), can increase the plasma concentration of hydrocodone, resulting in increased or prolonged opioid effects. These effects could be more pronounced with concomitant use of Hydrocodone Polistirex and Chlorpheniramine Polistirex and CYP2D6 and CYP3A4 inhibitors, particularly when an inhibitor is added after a stable dose of Hydrocodone Polistirex and Chlorpheniramine Polistirex is achieved [see Warnings and Precautions (5.7)]. After stopping a CYP3A4 inhibitor, as the effects of the inhibitor decline, the hydrocodone plasma concentration will decrease [see Clinical Pharmacology (12.3)], resulting in decreased opioid efficacy or a withdrawal syndrome in patients who had developed physical dependence to hydrocodone.

Avoid the use of Hydrocodone Polistirex and Chlorpheniramine Polistirex while taking a CYP3A4 or CYP2D6 inhibitor. If concomitant use is necessary, monitor patients for respiratory depression and sedation at frequent intervals.

7.3 CYP3A4 Inducers

The concomitant use of Hydrocodone Polistirex and Chlorpheniramine Polistirex and CYP3A4 inducers such as rifampin, carbamazepine, or phenytoin, can decrease the plasma concentration of hydrocodone [see Clinical Pharmacology (12.3)], resulting in decreased efficacy or onset of a withdrawal syndrome in patients who have developed physical dependence to hydrocodone [see Warnings and Precautions (5.7)]. After stopping a CYP3A4 inducer, as the effects of the inducer decline, the hydrocodone plasma concentration will increase [see Clinical Pharmacology (12.3)], which could increase or prolong both the therapeutic effects and adverse reactions, and may cause serious respiratory depression.

Avoid the use of Hydrocodone Polistirex and Chlorpheniramine Polistirex in patients who are taking CYP3A4 inducers. If concomitant use of a CYP3A4 inducer is necessary, follow the patient for reduced efficacy.

7.4 Phenytoin

Adverse event reports in the literature suggest a possible drug interaction involving increased serum phenytoin levels and phenytoin toxicity when chlorpheniramine and phenytoin are co-administered. The exact mechanism for this interaction is not known, however it is believed that chlorpheniramine may inhibit the hepatic metabolism of phenytoin. Avoid the use of Hydrocodone Polistirex and Chlorpheniramine Polistirex in patients who are taking phenytoin.

7.5 Benzodiazepines, and Other CNS Depressants

Due to additive pharmacologic effect, the concomitant use of benzodiazepines or other CNS depressants, including alcohol, other sedatives/hypnotics, anxiolytics, tranquilizers, muscle relaxants, general anesthetics, antipsychotics, and other opioids, can increase the risk of hypotension, respiratory depression, profound sedation, coma, and death. Avoid the use of Hydrocodone Polistirex and Chlorpheniramine Polistirex in patients who are taking benzodiazepines or other CNS depressants [see Warnings and Precautions (5.8)], and instruct patients to avoid consumption of alcohol while on Hydrocodone Polistirex and Chlorpheniramine Polistirex [see Drug Interactions (7.1), Patient Counseling Information (17)].

7.6 Serotonergic Drugs

The concomitant use of opioids with other drugs that affect the serotonergic neurotransmitter system has resulted in serotonin syndrome. If concomitant use is warranted, carefully observe the patient, particularly during treatment initiation. Discontinue Hydrocodone Polistirex and Chlorpheniramine Polistirex if serotonin syndrome is suspected.

7.7 Monoamine Oxidase Inhibitors (MAOIs)

Avoid the use of Hydrocodone Polistirex and Chlorpheniramine Polistirex in patients who are taking monoamine oxidase inhibitors (MAOIs) or have taken MAOIs within 14 days. The use of MAOIs or tricyclic antidepressants with hydrocodone, one of the active ingredients in Hydrocodone Polistirex and Chlorpheniramine Polistirex, may increase the effect of either the antidepressant or hydrocodone. MAOI interactions with opioids may manifest as serotonin syndrome or opioid toxicity (e.g., respiratory depression, coma).

7.8 Muscle Relaxants

Hydrocodone may enhance the neuromuscular blocking action of skeletal muscle relaxants and produce an increased degree of respiratory depression. Avoid the use of Hydrocodone Polistirex and Chlorpheniramine Polistirex in patients taking muscle relaxants. If concomitant use is necessary, monitor patients for signs of respiratory depression that may be greater than otherwise expected.

7.9 Diuretics

Opioids can reduce the efficacy of diuretics by inducing the release of antidiuretic hormone. Monitor patients for signs of diminished diuresis and/or effects on blood pressure and increase the dosage of the diuretic as needed.

7.10 Anticholinergic Drugs

The concomitant use of anticholinergic drugs with Hydrocodone Polistirex and Chlorpheniramine Polistirex may increase risk of urinary retention and/or severe constipation, which may lead to paralytic ileus [see Warnings and Precautions (5.9)].Monitor patients for signs of urinary retention or reduced gastric motility when Hydrocodone Polistirex and Chlorpheniramine Polistirex is used concomitantly with anticholinergic drugs.

Additive adverse effects resulting from cholinergic blockade (e.g., xerostomia, blurred vision, or constipation) may occur when anticholinergic drugs are administered with chlorpheniramine.

8 USE IN SPECIFIC POPULATIONS

8.1 Pregnancy

Risk Summary

Hydrocodone Polistirex and Chlorpheniramine Polistirex is not recommended for use in pregnant women, including during or immediately prior to labor.

Prolonged use of opioids during pregnancy may cause neonatal opioid withdrawal syndrome [see Warnings and Precautions (5.13), Clinical Considerations].

There are no available data with Hydrocodone Polistirex and Chlorpheniramine Polistirex use in pregnant women to inform a drug-associated risk for adverse developmental outcomes. Published studies with hydrocodone have reported inconsistent findings and have important methodological limitations (see Data).

Reproductive toxicity studies have not been conducted with Hydrocodone Polistirex and Chlorpheniramine Polistirex; however, studies are available with individual active ingredients or related active ingredients (see Data).

In animal reproduction studies, hydrocodone administered by the subcutaneous route to pregnant hamsters during the period of organogenesis produced a teratogenic effect at a dose approximately 70 times the maximum recommended human dose (MRHD) (see Data).

Chlorpheniramine administered by the oral route to mice throughout pregnancy was embryo lethal at a dose approximately 9 times the MRHD and decreased postnatal survival when dosing was continued after parturition. Chlorpheniramine administered by the oral route to male and female rats prior to mating produced embryolethality at a dose approximately 9 times the MRHD (see Data).

Based on the animal data, advise pregnant women of the potential risk to a fetus.

The estimated background risk of major birth defects and miscarriage for the indicated population is unknown. All pregnancies have a background risk of birth defect, loss, or other adverse outcomes. In the U.S. general population, the estimated background risk of major birth defects and miscarriage in clinically recognized pregnancies is 2 to 4% and 15 to 20%, respectively.

Clinical Considerations

Fetal/Neonatal Adverse Reactions

Prolonged use of opioid analgesics during pregnancy for medical or nonmedical purposes can result in physical dependence in the neonate and neonatal opioid withdrawal syndrome shortly after birth.

Neonatal opioid withdrawal syndrome presents as irritability, hyperactivity and abnormal sleep pattern, high pitched cry, tremor, vomiting, diarrhea and failure to gain weight. The onset, duration, and severity of neonatal opioid withdrawal syndrome vary based on the specific opioid used, duration of use, timing and amount of last maternal use, and rate of elimination of the drug by the newborn. Observe newborns for symptoms of neonatal opioid withdrawal syndrome and manage accordingly [see Warnings and Precautions (5.13)].

Labor or Delivery

Opioids cross the placenta and may produce respiratory depression and psycho-physiologic effects in neonates. An opioid antagonist, such as naloxone, must be available for reversal of opioid-induced respiratory depression in the neonate. Opioids, including Hydrocodone Polistirex and Chlorpheniramine Polistirex, can prolong labor through actions which temporarily reduce the strength, duration, and frequency of uterine contractions. However, this effect is not consistent and may be offset by an increased rate of cervical dilation, which tends to shorten labor. Monitor neonates exposed to opioids during labor for signs of excess sedation and respiratory depression.

Data

Human Data

Hydrocodone

A limited number of pregnancies have been reported in published observational studies and postmarketing reports describing hydrocodone use during pregnancy. However, these data cannot definitely establish or exclude any drug-associated risk during pregnancy. Methodological limitations of these observational studies include small sample size and lack of details regarding dose, duration and timing of exposure.

Chlorpheniramine

The majority of studies examining the use of chlorpheniramine in pregnancy did not find an association with an increased risk of congenital anomalies. In the few studies reporting an association, there was no consistent pattern of malformations noted.

Animal Data

Reproductive toxicity studies have not been conducted with Hydrocodone Polistirex and Chlorpheniramine Polistirex; however, studies are available with individual active ingredients or related active ingredients.

Hydrocodone

In an embryofetal development study in pregnant hamsters dosed on gestation day 8 during the period of organogenesis, hydrocodone induced cranioschisis, a malformation, at approximately 70 times the MRHD (on a mg/m^2 basis with a maternal subcutaneous dose of 102 mg/kg). Reproductive toxicology studies were also conducted with codeine, an opiate related to hydrocodone. In an embryofetal development study in pregnant rats dosed throughout the period of organogenesis, codeine increased resorptions and decreased fetal weights at a dose approximately 95 times the MRHD of hydrocodone (on a mg/m^2 basis with a maternal oral dose of codeine at 120 mg/kg/day); however, these effects occurred in the presence of maternal toxicity. In embryofetal development studies with pregnant rabbits and mice dosed throughout the period of organogenesis, codeine produced no adverse developmental effects at doses approximately 50 and 240 times, respectively, the MRHD of hydrocodone (on a mg/m^2 basis with maternal oral doses of codeine at 30 mg/kg/day in rabbits and 600 mg/kg/day in mice).

Chlorpheniramine

In embryofetal development studies with pregnant rats and rabbits dosed throughout the period of organogenesis, chlorpheniramine produced no adverse developmental effects at oral doses up to approximately 35 and 45 times, respectively, the MRHD on a mg/m^2 basis. However, in a reproduction study with pregnant mice dosed throughout pregnancy, chlorpheniramine produced embryolethality at a dose approximately 9 times the MRHD (on a mg/m^2 basis with a maternal oral dose of 20 mg/kg/day) and decreased postnatal survival when dosing was continued after parturition. In a fertility and reproduction study with male and female rats dosed prior to mating, chlorpheniramine produced embryolethality at a dose approximately 9 times the MRHD(on a mg/m^2 basis with an oral parental dose of 10 mg/kg/day).

8.2 Lactation

Risk Summary

Because of the potential for serious adverse reactions, including excess sedation, respiratory depression, and death in a breastfed infant, advise patients that breastfeeding is not recommended during treatment with Hydrocodone Polistirex and Chlorpheniramine Polistirex.

There are no data on the presence of Hydrocodone Polistirex and Chlorpheniramine Polistirex in human milk, the effects of Hydrocodone Polistirex and Chlorpheniramine Polistirex on the breastfed infant, or the effects of Hydrocodone Polistirex and Chlorpheniramine Polistirex on milk production; however, data are available with hydrocodone and chlorpheniramine.

Hydrocodone

Hydrocodone is present in breast milk. Published cases report variable concentrations of hydrocodone and hydromorphone (an active metabolite) in breast milk with administration of immediate-release hydrocodone to nursing mothers in the early post-partum period with relative infant doses of hydrocodone ranging between 1.4 and 3.7%. There are case reports of excessive sedation and respiratory depression in breastfed infants exposed to hydrocodone. No information is available on the effects of hydrocodone on milk production.

Chlorpheniramine

Chlorpheniramine is present in human milk. Chlorpheniramine has not been reported to cause effects on the breastfed infant. The published literature suggests that chlorpheniramine may decrease milk production based on its anticholinergic effects. (see Clinical Considerations)

Clinical Considerations

Infants exposed to Hydrocodone Polistirex and Chlorpheniramine Polistirex through breast milk should be monitored for excess sedation and respiratory depression. Withdrawal symptoms can occur in breastfed infants when maternal administration of an opioid is stopped, or when breastfeeding is stopped.

8.3 Females and Males of Reproductive Potential

Infertility

Chronic use of opioids, such as hydrocodone, a component of Hydrocodone Polistirex and Chlorpheniramine Polistirex, may cause reduced fertility in females and males of reproductive potential. It is not known whether these effects on fertility are reversible [see Adverse Reactions (6), Clinical Pharmacology (12.2)].

8.4 Pediatric Use

Hydrocodone Polistirex and Chlorpheniramine Polistirex is not indicated for use in patients younger than 18 years of age because the benefits of symptomatic treatment of cough associated with allergies or the common cold do not outweigh the risks for use of hydrocodone in these patients [see Indications (1), Warnings and Precautions (5.3)].

Life-threatening respiratory depression and death have occurred in children who received hydrocodone [see Warnings and Precautions (5.2)]. Because of the risk of life-threatening respiratory depression and death,Hydrocodone Polistirex and Chlorpheniramine Polistirex is contraindicated in children less than 6 years of age [see Contraindications (4)].

8.5 Geriatric Use

Clinical studies have not been conducted with Hydrocodone Polistirex and Chlorpheniramine Polistirex in geriatric populations.

Use caution when considering the use of Hydrocodone Polistirex and Chlorpheniramine Polistirex in patients 65 years of age or older. Elderly patients may have increased sensitivity to hydrocodone; greater frequency of decreased hepatic, renal, or cardiac function; or concomitant disease or other drug therapy [see Warnings and Precautions (5.4)].

Respiratory depression is the chief risk for elderly patients treated with opioids, including Hydrocodone Polistirex and Chlorpheniramine Polistirex. Respiratory depression has occurred after large initial doses of opioids were administered to patients who were not opioid-tolerant or when opioids were co-administered with other agents that depress respiration [see Warnings and Precautions (5.4, 5.8)].

Hydrocodone is known to be substantially excreted by the kidney, and the risk of adverse reactions to this drug may be greater in patients with impaired renal function. Because elderly patients are more likely to have decreased renal function, monitor these patients closely for respiratory depression, sedation, and hypotension.

8.6 Renal Impairment

The pharmacokinetics of Hydrocodone Polistirex and Chlorpheniramine Polistirex has not been characterized in patients with renal impairment. Patients with renal impairment may have higher plasma concentrations than those with normal function [see Clinical Pharmacology (12.3)]. Chlorpheniramine is cleared substantially by the kidney. As such, impaired renal function could potentially lead to the risk of decreased clearance and thereby increased retention or systemic levels of chlorpheniramine. Therefore, Hydrocodone Polistirex and Chlorpheniramine Polistirex should be used with caution in patients with severe impairment of renal function, and patients should be monitored closely for signs of hydrocodone toxicity (respiratory depression, sedation, and hypotension) and chlorpheniramine toxicity.

8.7 Hepatic Impairment

The pharmacokinetics of Hydrocodone Polistirex and Chlorpheniramine Polistirex has not been characterized in patients with hepatic impairment. Patients with severe hepatic impairment may have higher plasma concentrations than those with normal hepatic function [see Clinical Pharmacology (12.3)]. Chlorpheniramine is extensively metabolized by liver before elimination from the body. As such, impaired hepatic function could potentially lead to the risk of decreased metabolism and thereby increased systemic levels of chlorpheniramine. Therefore, Hydrocodone Polistirex and Chlorpheniramine Polistirex should be used with caution in patients with severe impairment of hepatic function, and patients should be monitored closely for signs of hydrocodone toxicity (respiratory depression, sedation, and hypotension) and chlorpheniramine toxicity.

9 DRUG ABUSE AND DEPENDENCE

9.1 Controlled Substance

Hydrocodone Polistirex and Chlorpheniramine Polistirex contains hydrocodone bitartrate, a Schedule II controlled substance.

9.2 Abuse

Hydrocodone

Hydrocodone Polistirex and Chlorpheniramine Polistirex contains hydrocodone, a substance with a high potential for abuse similar to other opioids including morphine and codeine. Hydrocodone Polistirex and Chlorpheniramine Polistirex can be abused and is subject to misuse, addiction, and criminal diversion [see Warnings and Precautions (5.1)].

All patients treated with opioids require careful monitoring for signs of abuse and addiction, since use of opioid analgesic and antitussive products carries the risk of addiction even under appropriate medical use.

Prescription drug abuse is the intentional non-therapeutic use of a prescription drug, even once, for its rewarding psychological or physiological effects.

Drug addiction is a cluster of behavioral, cognitive, and physiological phenomena that develop after repeated substance use and includes: a strong desire to take the drug, difficulties in controlling its use, persisting in its use despite harmful consequences, a higher priority given to drug use than to other activities and obligations, increased tolerance, and sometimes a physical withdrawal.

“Drug-seeking” behavior is very common in persons with substance use disorders. Drug-seeking tactics include emergency calls or visits near the end of office hours, refusal to undergo appropriate examination, testing, or referral, repeated “loss” of prescriptions, tampering with prescriptions, and reluctance to provide prior medical records or contact information for other treating health care provider(s). “Doctor shopping” (visiting multiple prescribers to obtain additional prescriptions) is common among drug abusers and people suffering from untreated addiction. Preoccupation with achieving adequate pain relief can be appropriate behavior in a patient with poor pain control.

Abuse and addiction are separate and distinct from physical dependence and tolerance. Health care providers should be aware that addiction may not be accompanied by concurrent tolerance and symptoms of physical dependence in all addicts. In addition, abuse of opioids can occur in the absence of true addiction.

Hydrocodone Polistirex and Chlorpheniramine Polistirex, like other opioids, can be diverted for non-medical use into illicit channels of distribution. Careful record-keeping of prescribing information, including quantity, frequency, and renewal requests, as required by state and federal law, is strongly advised.

Proper assessment of the patient, proper prescribing practices, periodic re-evaluation of therapy, and proper dispensing and storage are appropriate measures that help to limit abuse of opioid drugs.

Risks Specific to Abuse of Hydrocodone Polistirex and Chlorpheniramine Polistirex

Hydrocodone Polistirex and Chlorpheniramine Polistirex is for oral use only. Abuse of Hydrocodone Polistirex and Chlorpheniramine Polistirex poses a risk of overdose and death. The risk is increased with concurrent use of Hydrocodone Polistirex and Chlorpheniramine Polistirex with alcohol and other central nervous system depressants [see Warnings and Precautions (5.8), Drug Interactions (7.1, 7.5)].

Parenteral drug abuse is commonly associated with transmission of infectious diseases such as hepatitis and HIV.

9.3 Dependence

Psychological dependence, physical dependence, and tolerance may develop upon repeated administration of opioids; therefore, Hydrocodone Polistirex and Chlorpheniramine Polistirex should be prescribed and administered for the shortest duration that is consistent with individual patient treatment goals and patients should be reevaluated prior to refills [see Dosage and Administration (2.3), Warnings and Precautions (5.1)].

Physical dependence, the condition in which continued administration of the drug is required to prevent the appearance of a withdrawal syndrome, assumes clinically significant proportions only after several weeks of continued oral opioid use, although some mild degree of physical dependence may develop after a few days of opioid therapy.

If Hydrocodone Polistirex and Chlorpheniramine Polistirex is abruptly discontinued in a physically-dependent patient, a withdrawal syndrome may occur. Withdrawal also may be precipitated through the administration of drugs with opioid antagonist activity (e.g., naloxone, nalmefene), mixed agonist/antagonist analgesics (e.g., pentazocine, butorphanol, nalbuphine), or partial agonists (e.g., buprenorphine). Some or all of the following can characterize this syndrome: restlessness, lacrimation, rhinorrhea, yawning, perspiration, chills, myalgia, and mydriasis. Other signs and symptoms also may develop, including irritability, anxiety, backache, joint pain, weakness, abdominal cramps, insomnia, nausea, anorexia, vomiting, diarrhea, or increased blood pressure, respiratory rate, or heart rate.

Infants born to mothers physically dependent on opioids will also be physically dependent and may exhibit respiratory difficulties and withdrawal signs [see Use in Specific Populations (8.1)].

10 OVERDOSAGE

Clinical Presentation

Hydrocodone

Acute overdose with hydrocodone is characterized by respiratory depression (a decrease in respiratory rate and/or tidal volume, Cheyne-Stokes respiration, cyanosis), extreme somnolence progressing to stupor or coma, skeletal muscle flaccidity, cold and clammy skin, constricted pupils, and, in some cases, pulmonary edema, bradycardia, partial or complete airway obstruction, atypical snoring, hypotension, circulatory collapse, cardiac arrest, and death.

Hydrocodone may cause miosis, even in total darkness. Pinpoint pupils are a sign of opioid overdose but are not pathognomonic (e.g., pontine lesions of hemorrhagic or ischemic origin may produce similar findings). Marked mydriasis rather than miosis may be seen with hypoxia in overdose situations [see Clinical Pharmacology (12.2)].

Chlorpheniramine

Signs and symptoms of chlorpheniramine overdosage may vary from central nervous system depression to stimulation. Central toxic effects are characterized by agitation, anxiety, delirium, disorientation, hallucinations, hyperactivity, sedation, and seizures. Severe overdosage may produce coma, medullary paralysis, and death. Peripheral toxicity includes hypertension, tachycardia, dysrhythmias, vasodilation, hyperpyrexia, mydriasis, urinary retention, and diminished gastrointestinal motility. Atropine-like signs and symptoms (dry mouth, fixed dilated pupils, flushing, tachycardia, hallucinations, gastrointestinal symptoms, convulsions, urinary retention, cardiac arrhythmias and coma) may be observed.

Impaired secretion from sweat glands following toxic doses of drugs with anticholinergic side effects may predispose to hyperthermia.

Toxic psychosis, a possible class effect from overdose of sedating antihistamines, has been reported.

Treatment of Overdose

Treatment of overdosage is driven by the overall clinical presentation, and consists of discontinuation of Hydrocodone Polistirex and Chlorpheniramine Polistirex together with institution of appropriate therapy. Give primary attention to the institution of assisted or controlled ventilation. Employ other supportive measures (including oxygen and vasopressors) in the management of circulatory shock and pulmonary edema as indicated. Cardiac arrest or arrhythmias will require advanced life-support techniques. Gastric emptying may be useful in removing unabsorbed drug.

The opioid antagonists, naloxone and nalmefene, are specific antidotes for respiratory depression resulting from opioid overdose. For clinically significant respiratory or circulatory depression secondary to hydrocodone overdose, administer an opioid antagonist. An antagonist should not be administered in the absence of clinically significant respiratory depression. Because the duration of opioid reversal is expected to be less than the duration of action of hydrocodone in Hydrocodone Polistirex and Chlorpheniramine Polistirex , carefully monitor the patient until spontaneous respiration is reliably reestablished. Hydrocodone Polistirex and Chlorpheniramine Polistirex will continue to release hydrocodone and add to the hydrocodone load for 12 hours or longer following ingestion, necessitating prolonged monitoring. If the response to an opioid antagonist is suboptimal or only brief in nature, administer additional antagonist as directed by the product’s prescribing information.

Hemodialysis is not routinely used to enhance the elimination of hydrocodone or chlorpheniramine from the body.

Urinary excretion of chlorpheniramine is increased when the pH of the urine is acidic; however, acid diuresis is NOT recommended to enhance elimination in overdose, as the risks of acidemia and acute tubular necrosis in patients with rhabdomyolysis far outweigh any potential benefits.

11 DESCRIPTION

Hydrocodone Polistirex and Chlorpheniramine Polistirex Extended-Release Suspension contains hydrocodone, an opioid agonist; and chlorpheniramine, a histamine-1 (H1) receptor antagonist.

Each 5 mL of Hydrocodone Polistirex and Chlorpheniramine Polistirex Extended-Release (ER) Suspension contains hydrocodone polistirex equivalent to 10 mg of hydrocodone bitartrate and chlorpheniramine polistirex equivalent to 8 mg of chlorpheniramine maleate. Hydrocodone is a centrally-acting narcotic antitussive. Chlorpheniramine is an antihistamine.

Hydrocodone Polistirex and Chlorpheniramine Polistirex ER Suspension is for oral use only.

Hydrocodone Polistirex and Chlorpheniramine Polistirex Extended-Release Suspension also contains the following inactive ingredients: Ascorbic acid, D&C Yellow No. 10, flavors, high fructose corn syrup, modified food starch, methylparaben, polysorbate 80, polyvinyl acetate, propylene glycol, propylparaben, purified water, sodium ascorbate, sodium metabisulfite, sodium polystyrene sulfonate, sucrose, triacetin, xanthan gum.

Hydrocodone Polistirex

The chemical name for hydrocodone, a centrally-acting narcotic antitussive, is 4,5α-epoxy-3-methoxy-17- methylmorphinan-6-one. Hydrocodone polistirex is a complex of sulfonated styrene-divinylbenzene copolymer. The molecular weight for hydrocodone and the polistirex resin is 298.364 g/mol and n x 315 g/mol- 1, respectively. The molecular formula for hydrocodone and the polistirex resin is C18H21NO3 and (C18SO3H19)n, respectively. It has the following structural formula:

Structure 1

Chlorpheniramine Polistirex

The chemical name for chlorpheniramine, an antihistamine, is 2-[p-chloro-α-[2-(dimethylamino)ethyl]- benzyl]pyridine. Chlorpheniramine polistirex is a complex of sulfonated styrene-divinylbenzene copolymer. The molecular weight for chlorpheniramine and the polistirex resin is 274.79 g/mol and n x 315 g/mol-1, respectively. The molecular formula for chlorpheniramine and the polistirex resin is C16N2H19Cl and (C18SO3H19)n, respectively. It has the following structural formula:

structure 2

12 CLINICAL PHARMACOLOGY

12.1 Mechanism of Action

Hydrocodone

Hydrocodone is an opioid agonist with relative selectivity for the mu-opioid receptor, although it can interact with other opioid receptors at higher doses. The precise mechanism of action of hydrocodone and other opiates is not known; however, hydrocodone is believed to act centrally on the cough center. In excessive doses, hydrocodone will depress respiration.

Chlorpheniramine

Chlorpheniramine is a propylamine derivative antihistamine (H1-receptor antagonist) of the alkylamine class that also possesses anticholinergic and sedative activity. It prevents released histamine from dilating capillaries and causing edema of the respiratory mucosa.

12.2 Pharmacodynamics

Hydrocodone

Effects on the Central Nervous System

Hydrocodone produces respiratory depression by direct action on brain stem respiratory centers. The respiratory depression involves a reduction in the responsiveness of the brain stem respiratory centers to both increases in carbon dioxide tension and to electrical stimulation.

Hydrocodone causes miosis, even in total darkness. Pinpoint pupils are a sign of opioid overdose but are not pathognomonic (e.g., pontine lesions of hemorrhagic or ischemic origins may produce similar findings). Marked mydriasis rather than miosis may be seen due to hypoxia in overdose situations.

Effects on the Gastrointestinal Tract and Other Smooth Muscle

Hydrocodone causes a reduction in motility associated with an increase in smooth muscle tone in the antrum of the stomach and duodenum. Digestion of food in the small intestine is delayed and propulsive contractions are decreased. Propulsive peristaltic waves in the colon are decreased, while tone may be increased to the point of spasm resulting in constipation. Other opioid-induced effects may include a reduction in biliary and pancreatic secretions, spasm of sphincter of Oddi, and transient elevations in serum amylase.

Effects on the Cardiovascular System

Hydrocodone produces peripheral vasodilation which may result in orthostatic hypotension or syncope. Manifestations of histamine release and/or peripheral vasodilation may include pruritus, flushing, red eyes and sweating and/or orthostatic hypotension.

Effects on the Endocrine System

Opioids inhibit the secretion of adrenocorticotropic hormone (ACTH), cortisol, and luteinizing hormone (LH) in humans [see Adverse Reactions (6)]. They also stimulate prolactin, growth hormone (GH) secretion, and pancreatic secretion of insulin and glucagon.

Chronic use of opioids may influence the hypothalamic-pituitary-gonadal axis, leading to androgen deficiency that may manifest as low libido, impotence, erectile dysfunction, amenorrhea, or infertility. The causal role of opioids in the clinical syndrome of hypogonadism is unknown because the various medical, physical, lifestyle, and psychological stressors that may influence gonadal hormone levels have not been adequately controlled for in studies conducted to date [see Adverse Reactions (6)].

Effects on the Immune System

Opioids have been shown to have a variety of effects on components of the immune system in in vitro and animal models. The clinical significance of these findings is unknown. Overall, the effects of opioids appear to be modestly immunosuppressive.

Concentration–Adverse Reaction Relationships

There is a relationship between increasing hydrocodone plasma concentration and increasing frequency of dose related opioid adverse reactions such as nausea, vomiting, CNS effects, and respiratory depression. In opioid tolerant patients, the situation may be altered by the development of tolerance to opioid-related adverse reactions.

12.3 Pharmacokinetics

Absorption

Following multiple dosing with Hydrocodone Polistirex and Chlorpheniramine Polistirex, hydrocodone mean (S.D.) peak plasma concentrations of 22.8 (5.9) ng/mL occurred at 3.4 hours. Food has no significant effect on the extent of absorption of hydrocodone.

Chlorpheniramine mean (S.D.) peak plasma concentrations of 58.4 (14.7) ng/mL occurred at 6.3 hours following multiple dosing.

Distribution

Although the extent of protein binding of hydrocodone in human plasma has not been definitively determined, structural similarities to related opioid analgesics suggest that hydrocodone is not extensively protein bound. As most agents in the 5-ring morphinan group of semi-synthetic opioids bind plasma protein to a similar degree (range 19% [hydromorphone] to 45% [oxycodone]), hydrocodone is expected to fall within this range.

Chlorpheniramine is widely distributed throughout the tissues of the body, including the central nervous system. It reportedly has an apparent steady-state volume of distribution of approximately 3.2 L/kg in adults and children and is about 70% bound to plasma proteins. Chlorpheniramine and its metabolites likely cross the placental barrier and are excreted into human breast milk.

Elimination

Metabolism

Hydrocodone exhibits a complex pattern of metabolism, including N-demethylation, O-demethylation, and 6keto reduction to the corresponding 6-α-and 6-β-hydroxy metabolites. CYP3A4 mediated N-demethylation to norhydrocodone is the primary metabolic pathway of hydrocodone with a lower contribution from CYP2D6 mediated O-demethylation to hydromorphone. Hydromorphone is formed from the O-demethylation of hydrocodone and may contribute to the total analgesic effect of hydrocodone. Therefore, the formation of these and related metabolites can, in theory, be affected by other drugs [see Drug Interactions (7)]. Published in vitro studies have shown that N-demethylation of hydrocodone to form norhydrocodone can be attributed to CYP3A4 while O-demethylation of hydrocodone to hydromorphone is predominantly catalyzed by CYP2D6 and to a lesser extent by an unknown low affinity CYP enzyme.

Chlorpheniramine is rapidly and extensively metabolized via demethylation in the liver, forming mono-and didesmethyl derivatives. Oxidative metabolism of chlorpheniramine is catalyzed by cytochrome P-450 2D6.

Excretion

Hydrocodone and its metabolites are eliminated primarily in the kidneys. The mean plasma half-life of hydrocodone is approximately 4 hours.

Chlorpheniramine and its metabolites are primarily excreted through the kidneys, with large individual variation. Urinary excretion depends on urine pH and flow rate. The mean plasma half-life of chlorpheniramine is approximately 21 to 24 hours.

13 NONCLINICAL TOXICOLOGY

13.1 Carcinogenesis and Mutagenesis and Impairment of Fertility

Carcinogenicity, mutagenicity, and fertility studies have not been conducted with Hydrocodone Polistirex and Chlorpheniramine Polistirex; however, published information is available for the individual active ingredients or related active ingredients.

Hydrocodone

Carcinogenicity studies were conducted with codeine, an opiate related to hydrocodone. Two-year studies in F344/N rats and B6C3F1 mice were conducted to assess the carcinogenic potential of codeine. No evidence of tumorigenicity was observed in male and female rats at codeine dietary doses up to 70 and 80 mg/kg/day (approximately equivalent to 55 and 65 times the MRHD of hydrocodone on a mg/m^2 basis, respectively). No evidence of tumorigenicity was observed in male and female mice at codeine dietary doses up to 400 mg/kg/day (approximately equivalent to 160 times the MRHD of hydrocodone on a mg/m^2 basis). Mutagenicity studies with hydrocodone have not been conducted. Fertility studies with hydrocodone have not been conducted.

Chlorpheniramine

Carcinogenicity studies were conducted with chlorpheniramine maleate. Two-year studies in F344/N rats and B6C3F1 mice were conducted to assess the carcinogenic potential of chlorpheniramine. No evidence of tumorigenicity was observed in male and female rats at chlorpheniramine oral doses up to 30 and 60 mg/kg/day for 5 days/week (approximately equivalent to 25 and 50 times the MRHD on a mg/m^2 basis, respectively). No evidence of tumorigenicity was observed in male and female mice at chlorpheniramine oral doses up to 50 and 200 mg/kg/day for 5 days/week (approximately equivalent to 20 and 85 times the MRHD on a mg/m^2 basis, respectively).

Chlorpheniramine maleate was not mutagenic in the in vitro bacterial reverse mutation assay or the in vitro mouse lymphoma forward mutation assay. Chlorpheniramine maleate was clastogenic in the in vitro Chinese hamster ovary (CHO) cell chromosomal aberration assay.

Chlorpheniramine maleate had no effects on fertility in rats and rabbits at oral doses approximately 35 and 45 times the MRHD on a mg/m^2 basis, respectively.

16 HOW SUPPLIED/STORAGE AND HANDLING

Hydrocodone Polistirex and Chlorpheniramine Polistirex Extended-Release Suspension, equivalent to 10 mg hydrocodone bitartrate and 8 mg chlorpheniramine maleate per 5 mL, is a yellow viscous suspension.

NDC 72162-1283-7 3 fl. oz. bottle containing 70 mL suspension.

NDC 72162-1283-4 16 fl. oz. bottle containing 473 mL suspension.

NDC 72162-1283-2 4 fl. oz. bottle containing 115 mL suspension.

Shake well. Dispense in a tight, light-resistant container, as defined in the USP, with a child-resistant closure.

Light Sensitive: Protect from light. Store away from direct sunlight.

Store at 20°C to 25°C (68°F to 77°F); excursions permitted to 15°C to 30°C (59°F to 86°F) [see USP Controlled Room Temperature.]

Ensure that patients have an oral dosing dispenser that measures the appropriate volume in milliliters. Counsel patients on how to utilize the oral dosing dispenser and correctly measure the oral suspension as prescribed.

Repackaged/Relabeled by:
Bryant Ranch Prepack, Inc.
Burbank, CA 91504

17 PATIENT COUNSELING INFORMATION

Advise the patient to read the FDA-approved patient labeling (Medication Guide).

Addiction, Abuse, and Misuse

Inform patients that the use of Hydrocodone Polistirex and Chlorpheniramine Polistirex Extended-Release Suspension, even when taken as recommended, can result in addiction, abuse, and misuse, which can lead to overdose and death [see Warnings and Precautions (5.1)]. Instruct patients not to share Hydrocodone Polistirex and Chlorpheniramine Polistirex Extended-Release Suspension with others and to take steps to protect Hydrocodone Polistirex and Chlorpheniramine Polistirex Extended-Release Suspension from theft or misuse.

Important Dosing and Administration Instructions

Instruct patients how to measure and take the correct dose of Hydrocodone Polistirex and Chlorpheniramine Polistirex Extended-Release Suspension. Advise patients to measure Hydrocodone Polistirex and Chlorpheniramine Polistirex Extended-Release Suspension with an accurate milliliter measuring device. Patients should be informed that a household teaspoon is not an accurate measuring device and could lead to overdosage. Advise patients to ask their pharmacist to recommend an appropriate measuring device and for instructions for measuring the correct dose [see Dosage and Administration (2.1) and Warnings and Precautions (5.5)]. Advise patients not to increase the dose or dosing frequency of Hydrocodone Polistirex and Chlorpheniramine Polistirex Extended-Release Suspension because serious adverse events such as respiratory depression may occur with overdosage [see Warnings and Precautions (5.2) and Overdosage (10)].

Life-Threatening Respiratory Depression

Inform patients of the risk of life-threatening respiratory depression, including information that the risk is greatest when starting Hydrocodone Polistirex and Chlorpheniramine Polistirex and that it can occur even at recommended dosages [see Warnings and Precautions (5.2)]. Advise patients how to recognize respiratory depression and to seek medicalattention if breathing difficulties develop.

Accidental Ingestion

Inform patients that accidental ingestion, especially by children, may result in respiratory depression or death [see Warnings and Precautions (5.2)]. Instruct patients to take steps to store Hydrocodone Polistirex and Chlorpheniramine Polistirex Extended-Release Suspension securely and to properly dispose of unused Hydrocodone Polistirex and Chlorpheniramine Polistirex Extended-Release Suspension in accordance with the local state guidelines and/or regulations.

Activities Requiring Mental Alertness

Advise patients to avoid engaging in hazardous tasks that require mental alertness and motor coordination such as operating machinery or driving a motor vehicle as Hydrocodone Polistirex and Chlorpheniramine Polistirex Extended-Release Suspension may produce marked drowsiness [see Warnings and Precautions (5.6)].

Interactions with Benzodiazepines and Other Central Nervous System Depressants, Including Alcohol

Inform patients and caregivers that potentially fatal additive effects may occur if Hydrocodone Polistirex and Chlorpheniramine Polistirex Extended-Release Suspension is used with benzodiazepines or other CNS depressants, including alcohol. Advise patients to avoid concomitant use of Hydrocodone Polistirex and Chlorpheniramine Polistirex Extended-Release Suspension with benzodiazepines or other CNS depressants and instruct patients not to consume alcoholic beverages, as well as prescription and over-the-counter products that contain alcohol, during treatment with Hydrocodone Polistirex and Chlorpheniramine Polistirex Extended-Release Suspension [see Warnings and Precautions (5.8), Drug Interactions (7.1, 7.5)].

Constipation

Advise patients of the potential for severe constipation [see Warnings and Precautions (5.9), Adverse Reactions (6)].

Anaphylaxis

Inform patients that anaphylaxis has been reported with ingredients contained in Hydrocodone Polistirex and Chlorpheniramine Polistirex. Advise patients how to recognize such a reaction and when to seek medical attention [see Contraindications (4), Adverse Reactions (6)].

MAOI Interaction

Inform patients not to take Hydrocodone Polistirex and Chlorpheniramine Polistirex while using or within 14 days of stopping any drugs that inhibit monoamine oxidase. Patients should not start MAOIs while taking Hydrocodone Polistirex and Chlorpheniramine Polistirex [see Drug Interactions (7.7)].

Hypotension

Inform patients that Hydrocodone Polistirex and Chlorpheniramine Polistirex may cause orthostatic hypotension and syncope. Instruct patients how to recognize symptoms of low blood pressure and how to reduce the risk of serious consequences should hypotension occur (e.g., sit or lie down, carefully rise from a sitting or lying position) [see Warnings and Precautions (5.12)].

Pregnancy

Advise patients that use of Hydrocodone Polistirex and Chlorpheniramine Polistirex is not recommended during pregnancy [see Use in Specific Populations (8.1)].

Neonatal Opioid Withdrawal Syndrome

Inform female patients of reproductive potential that use of Hydrocodone Polistirex and Chlorpheniramine Polistirex during pregnancy can result in neonatal opioid withdrawal syndrome, which may be life-threatening if not recognized and treated [see Warnings and Precautions (5.13), Use in Specific Populations (8.1)].

Embryo-Fetal Toxicity

Inform female patients of reproductive potential that Hydrocodone Polistirex and Chlorpheniramine Polistirex can cause fetal harm and to inform their healthcare provider of a known or suspected pregnancy [see Use in Specific Populations (8.1)].

Lactation

Advise women that breastfeeding is not recommended during treatment with Hydrocodone Polistirex and Chlorpheniramine Polistirex [see Use in Specific Populations (8.2)].

Infertility

Inform patients that chronic use of opioids, such as hydrocodone, a component of Hydrocodone Polistirex and Chlorpheniramine Polistirex, may cause reduced fertility. It is not known whether these effects on fertility are reversible [see Use in Specific Populations (8.3)].

Adrenal Insufficiency

Inform patients that Hydrocodone Polistirex and Chlorpheniramine Polistirex could cause adrenal insufficiency, a potentially life-threatening condition. Adrenal insufficiency may present with non-specific symptoms and signs such as nausea, vomiting, anorexia, fatigue, weakness, dizziness, and low blood pressure. Advise patients to seek medical attention if they experience a constellation of these symptoms [see Warnings and Precautions (5.14)].

Serotonin Syndrome

Inform patients that Hydrocodone Polistirex and Chlorpheniramine Polistirex could cause a rare but potentially life-threatening condition resulting from concomitant administration of serotonergic drugs. Warn patients of the symptoms of serotonin syndrome and to seek medical attention right away if symptoms develop. Instruct patients to inform their physicians if they are taking, or plan to take serotonergic medications. [see Adverse Reactions (6), Drug Interactions (7.6)].

Disposal of Unused Hydrocodone Polistirex and Chlorpheniramine Polistirex

Advise patients to properly dispose of unused Hydrocodone Polistirex and Chlorpheniramine Polistirex. Advise patients to throw the drug in the household trash following these steps. 1) Remove them from their original containers and mix them with an undesirable substance, such as used coffee grounds or kitty litter (this makes the drug less appealing to children and pets, and unrecognizable to people who may intentionally go through the trash seeking drugs). 2) Place the mixture in a sealable bag, empty can, or other container to prevent the drug from leaking or breaking out of a garbage bag, or to dispose of in accordance with local state guidelines and/or regulations.

Manufactured by:
Tris Pharma, Inc.
Monmouth Junction, NJ 08852
LB8535 Rev. 03 05/2021

MEDICATION GUIDE

Hydrocodone Polistirex and
Chlorpheniramine Polistirex
Extended-Release Suspension, C-II
(hye” droe koe’ done pol” i stye’ rex and
klor” fen ir’ a mean pol” i stye’ rex)

What is the most important information I should know about Hydrocodone Polistirex and Chlorpheniramine Polistirex?

Hydrocodone Polistirex and Chlorpheniramine Polistirex is not for children under 18 years of age.

Hydrocodone Polistirex and Chlorpheniramine Polistirex can cause serious side effects, including:

- Addiction, abuse and misuse. Taking Hydrocodone Polistirex and Chlorpheniramine Polistirex or other medicines that contain an opioid can cause addiction, abuse and misuse, which can lead to overdose and death. This can happen even if you take Hydrocodone Polistirex and Chlorpheniramine Polistirex exactly as prescribed by your healthcare provider. Your risk of addiction, abuse, and misuse is increased if you or a family member has a history of drug or alcohol abuse or addiction, or mental health problems.

- Do not share your Hydrocodone Polistirex and Chlorpheniramine Polistirex with other people.
- Keep Hydrocodone Polistirex and Chlorpheniramine Polistirex in a safe place away from children.

- Life-threatening breathing problems (respiratory depression). Hydrocodone Polistirex and Chlorpheniramine Polistirex can cause breathing problems (respiratory depression) that can happen at any time during treatment and can lead to death. Your risk of breathing problems is greatest when you first start taking Hydrocodone Polistirex and Chlorpheniramine Polistirex, are taking other medicines that can cause breathing problems, have certain lung problems, are elderly, or have certain other health problems.
  Children are at higher risk for respiratory depression. Breathing problems can happen even if you take Hydrocodone Polistirex and Chlorpheniramine Polistirex exactly as prescribed by your healthcare provider.
  Call your healthcare provider or get emergency medical help right away if anyone taking Hydrocodone Polistirex and Chlorpheniramine Polistirex
  has any of the symptoms below:

- increased sleepiness

- confusion
- difficulty breathing
- shallow breathing
- limpness
  Keep Hydrocodone Polistirex and Chlorpheniramine Polistirex in a safe place away from children. Accidental use of even 1 dose of Hydrocodone Polistirex and Chlorpheniramine Polistirex, especially by a child, is a medical emergency and can cause breathing problems (respiratory depression) which can lead to death. If a child accidentally takes Hydrocodone Polistirex and Chlorpheniramine Polistirex, get emergency medical help right away.
  - Overdose and death due to medicine dosing errors. Overdose and death can happen if you measure the wrong dose of Hydrocodone Polistirex and Chlorpheniramine Polistirex. Always use an accurate milliliter measuring device to measure the correct amount of Hydrocodone Polistirex and Chlorpheniramine Polistirex. Do not use a household teaspoon to measure your medicine. You may accidentally take too much. You can ask your pharmacist for the measuring device you should use and how to measure the correct dose.
  - Breathing problems (respiratory depression) that can lead to death and opioid withdrawal can happen if you start taking or stop taking other medicines while taking Hydrocodone Polistirex and Chlorpheniramine Polistirex, including:
  - certain antibiotics
  - certain medicines to treat a fungal infection
  - certain medicines to treat Human Immunodeficiency Virus (HIV)-1 infection, Acquired Immune Deficiency
  - Syndrome (AIDS), or Hepatitis C
  - rifampin
  - carbamazepine
  - phenytoin

What is Hydrocodone Polistirex and Chlorpheniramine Polistirex Extended-Release Suspension?

- Hydrocodone Polistirex and Chlorpheniramine Polistirex is a prescription medicine used in adults to treat cough and upper respiratory symptoms that you can have with allergies or a common cold. Hydrocodone Polistirex and Chlorpheniramine Polistirex contains 2 medicines, hydrocodone and chlorpheniramine. Hydrocodone is an opioid (narcotic) cough suppressant. Chlorpheniramine is an antihistamine.
- Hydrocodone Polistirex and Chlorpheniramine Polistirex is a federal controlled substance (CII) because it contains hydrocodone that can be abused or lead to dependence. Keep Hydrocodone Polistirex and Chlorpheniramine Polistirex in a safe place to prevent misuse and abuse. Selling or giving away Hydrocodone Polistirex and Chlorpheniramine Polistirex may harm others, and is against the law. Tell your healthcare provider if you have abused or been dependent on alcohol, prescription medicines or street drugs.

Who should not take Hydrocodone Polistirex and Chlorpheniramine Polistirex?

Hydrocodone Polistirex and Chlorpheniramine Polistirex is not for children under 18 years of age. See “What is the most important information I should know about Hydrocodone Polistirex and Chlorpheniramine Polistirex?”

Do not take Hydrocodone Polistirex and Chlorpheniramine Polistirex if you:

- have severe breathing problems (respiratory depression) or breathing problems caused by asthma. See “What is the most important information I should know about Hydrocodone Polistirex and Chlorpheniramine Polistirex?”
- have a blockage (obstruction) in your bowel such as a paralytic ileus.
- are allergic to hydrocodone, chlorpheniramine, or any of the ingredients in Hydrocodone Polistirex and Chlorpheniramine Polistirex. See the end of this Medication Guide for a complete list of ingredients.

Ask your healthcare provider if you have any questions about this information.

Before you take Hydrocodone Polistirex and Chlorpheniramine Polistirex, tell your healthcare provider about all of your medical conditions, including if you:.

- have a drug addiction

- have lung or breathing problems

- have a fever and are coughing up mucus

- have had a recent head injury

- have had a brain tumor or other brain problems

- have or have had seizures

- have pain in your stomach-area (abdomen)
- have constipation or bowel problem
- have bile duct or pancreas problems
- have prostate problems
- have problems with your urinary tract or difficulty urinating

- have kidney or liver problems
- have adrenal gland problems
- have low blood pressure

- plan to have surgery

- are pregnant or plan to become pregnant. Hydrocodone Polistirex and Chlorpheniramine Polistirex can harm your unborn baby. See “What is the most important information I should know about Hydrocodone Polistirex and Chlorpheniramine Polistirex?”
- are breastfeeding or plan to breastfeed. Hydrocodone and chlorpheniramine pass into your breast milk and can cause serious side effects in your baby including increased sleepiness, breathing problems (respiratory depression), and death. You and your healthcare provider should decide if you will take Hydrocodone Polistirex and Chlorpheniramine Polistirex or breastfeed. You should not do both. See “What should I avoid while taking Hydrocodone Polistirex and Chlorpheniramine Polistirex?”
- plan to have children. Hydrocodone Polistirex and Chlorpheniramine Polistirex may affect the ability to have a child in females and males (fertilityproblems). It is not known if these fertility problems will be reversible, even after you stop taking Hydrocodone Polistirex and Chlorpheniramine Polistirex. Talk to your healthcare provider if this is a concern for you.

Tell your healthcare provider about all the medicines you take, including prescription and over-the-counter medicines, vitamins, and herbal supplements.

Taking Hydrocodone Polistirex and Chlorpheniramine Polistirex with certain other medicines can cause side effects or affect how well Hydrocodone Polistirex and Chlorpheniramine Polistirex or the other medicines work. Do not start or stop taking other medicines without talking to your healthcare provider.

Especially tell your healthcare provider if you:

- See “What should I avoid while taking Hydrocodone Polistirex and Chlorpheniramine Polistirex?”
- take pain medicines such as opioids (narcotics).
- take cold or allergy medicines that contain antihistamines or cough suppressants.
- drink alcohol.
- take muscle relaxants.
- take certain medicines used to treat mood, anxiety, psychotic or thought disorders, or depression, including monoamine oxidase inhibitors (MAOIs), tricyclics, selective serotonin reuptake inhibitors (SSRIs), selective serotonin nnorepinephrine reuptake inhibitors (SNRIs), or antipsychotics.
- take medicines to lower your blood pressure.
- take water pills (diuretics).
- take medicines called “anticholinergics” used to treat health problems such as asthma, chronic obstructive pulmonarydisease (COPD), or stomach problems.
- take a medicine called “phenytoin” used to treat seizures or epilepsy.

Ask your healthcare provider if you are not sure if you take any of these medicines.

How should I take Hydrocodone Polistirex and Chlorpheniramine Polistirex?

- See “What is the most important information I should know about Hydrocodone Polistirex and Chlorpheniramine Polistirex?”
- Take Hydrocodone Polistirex and Chlorpheniramine Polistirex exactly as your healthcare provider tells you to take it. Do not change your dosewithout talking to your healthcare provider.
- Take Hydrocodone Polistirex and Chlorpheniramine Polistirex by mouth only.
- Take Hydrocodone Polistirex and Chlorpheniramine Polistirex using an accurate milliliter measuring device. . Only measure Hydrocodone Polistirex and Chlorpheniramine Polistirex Extended-Release Suspension with the dosing cup that comes with your prescription. If you do not have a device, ask your pharmacist to give you a measuring device to help you measure the correct amount of Hydrocodone Polistirex and Chlorpheniramine Polistirex. Do not use a household teaspoon to measure your medicine. You may accidentally take too much.

- The dosing cup is calibrated for measuring 2.5 mL and 5 mL dosages. Find the marked line for the dose you are taking.
- Fill the cup so the medicine is leveled to the dose that has been prescribed. Do not fill over the dosage line.

- Do not overfill the measuring device.
- Rinse the measuring device with water after each use.
  Cup
- If you take too much Hydrocodone Polistirex and Chlorpheniramine Polistirex, call your healthcare provider or go to the nearest hospital emergency room right away.
- Tell your healthcare provider if your cough does not get better within 5 days of treatment with Hydrocodone Polistirex and Chlorpheniramine Polistirex.

What should I avoid while taking Hydrocodone Polistirex and Chlorpheniramine Polistirex?

- Avoid driving a car or operating machinery during treatment with Hydrocodone Polistirex and Chlorpheniramine Polistirex. Hydrocodone Polistirex and Chlorpheniramine Polistirex can cause you to be drowsy, slow your thinking and motor skills, and may affect your vision.
- Do not drink alcohol during treatment with Hydrocodone Polistirex and Chlorpheniramine Polistirex. Drinking alcohol can increase your chances of having serious side effects.

Avoid the use of Hydrocodone Polistirex and Chlorpheniramine Polistirex if you:

- are pregnant. Use of Hydrocodone Polistirex and Chlorpheniramine Polistirex during pregnancy can cause withdrawal symptoms in your newborn baby that could be life-threatening if not recognized and treated. Tell your healthcare provider right away if you are pregnant or think you may be pregnant.
- are breastfeeding. Use of Hydrocodone Polistirex and Chlorpheniramine Polistirex while breastfeeding can cause severe breathing problems (respiratory depression) in your breastfed infant that could be life-threatening.
- take a medicine called a monoamine oxidase inhibitor (MAOI). Avoid taking an MAOI within 14 days after you stop taking Hydrocodone Polistirex and Chlorpheniramine Polistirex. Avoid starting Hydrocodone Polistirex and Chlorpheniramine Polistirex if you stopped taking an MAOI in the last 14 days.

What are the possible side effects of Hydrocodone Polistirex and Chlorpheniramine Polistirex? Hydrocodone Polistirex and Chlorpheniramine Polistirex can cause serious side effects, including:

- See “What is the most important information I should know about Hydrocodone Polistirex and Chlorpheniramine Polistirex?”
- Bowel problems including severe constipation or stomach pain. See “Who should not take Hydrocodone Polistirex and Chlorpheniramine Polistirex?”
- Increased pressure in your head (intracranial). Avoid the use of Hydrocodone Polistirex and Chlorpheniramine Polistirex if you have a head injury or have been told that you have changes in the tissue of your brain (brain lesions) or increased pressure in your head.
- Increased risk of seizures in people with seizure disorders. If you have a seizure disorder, Hydrocodone Polistirex and Chlorpheniramine Polistirex may increase how often you have a seizure.
- Low blood pressure. A sudden drop in blood pressure can happen in some people during treatment with Hydrocodone Polistirex and Chlorpheniramine Polistirex and this may cause you to feel dizzy, faint, lightheaded, or weak, especially when you stand up (orthostatic hypotension). Your risk of having this problem may be increased if you take Hydrocodone Polistirex and Chlorpheniramine Polistirex with certain other medicines that lower blood pressure. If you have any of these symptoms while taking Hydrocodone Polistirex and Chlorpheniramine Polistirex, sit or lie down. Do not change your body position too fast. Get up slowly from sitting or lying down.

Adrenal gland problems. Hydrocodone Polistirex and Chlorpheniramine Polistirex can cause serious and life-threatening adrenal gland problems. Your healthcare provider may do blood tests to check for adrenal gland problems. Call your healthcare provider right away if you have any of these symptoms:

- nausea
- vomiting

- not wanting to eat (anorexia)
- fatigue
- weakness
- dizziness
- low blood pressure

The most common side effects of Hydrocodone Polistirex and Chlorpheniramine Polistirex include:

- sleepiness
- confusion
- coordination problems
- decrease in mental and physical performance
- lack of energy
- lightheadedness
- dizziness
- headache
- dry mouth
- nausea
- vomiting
- constipation

These are not all the possible side effects of Hydrocodone Polistirex and Chlorpheniramine Polistirex.
Call your doctor for medical advice about side effects. You may report side effects to FDA at 1-800-FDA-1088.

How should I store Hydrocodone Polistirex and Chlorpheniramine Polistirex?

- Store Hydrocodone Polistirex and Chlorpheniramine Polistirex at room temperature between 68°F to 77°F (20°C to 25°C).
- Store Hydrocodone Polistirex and Chlorpheniramine Polistirex in a tightly closed container, in a dry, cool place away from heat or direct sunlight.
- Keep Hydrocodone Polistirex and Chlorpheniramine Polistirex Extended-Release Suspension and all medicines out of the reach of children.

How should I dispose of Hydrocodone Polistirex and Chlorpheniramine Polistirex?

Remove unused Hydrocodone Polistirex and Chlorpheniramine Polistirex from the container and mix it with an undesirable, non-toxic substance such as cat litter or used coffee grounds to make it less appealing to children and pets. Place the mixture in a container such as a sealed plastic bag and throw it away in the household trash. You can also follow your state or local guidelines on how to safely throw away Hydrocodone Polistirex and Chlorpheniramine Polistirex.

General information about the safe and effective use of Hydrocodone Polistirex and Chlorpheniramine Polistirex.

Medicines are sometimes prescribed for purposes other than those listed in a Medication Guide. Do not use Hydrocodone Polistirex and Chlorpheniramine Polistirex for a condition for which it was not prescribed. Do not give Hydrocodone Polistirex and Chlorpheniramine Polistirex to other people, even if they have the same symptoms that you have. It may harm them.

You can ask your pharmacist or healthcare provider for information about Hydrocodone Polistirex and Chlorpheniramine Polistirex that is written for health professionals.

What are the ingredients in Hydrocodone Polistirex and Chlorpheniramine Polistirex?

Active Ingredients: hydrocodone polistirex and chlorpheniramine polistirex

Inactive Ingredients: ascorbic acid, D&C Yellow No. 10, flavors, high fructose corn syrup, modified food starch, methylparaben, polysorbate 80, polyvinyl acetate, propylene glycol, propylparaben, purified water, sodium ascorbate, sodium metabisulfite, sodium polystyrene sulfonate, sucrose, triacetin, xanthan gum

Manufactured by:
Tris Pharma, Inc.
Monmouth Junction, NJ 08852
LB8535 Rev. 03 05/2021

This Medication Guide has been approved by the U.S. Food and Drug Administration. Revised: July 2018

PACKAGE LABEL

Hydrocodone Poli/ Chlorphe CII Susp 473 mL

Extended Label